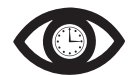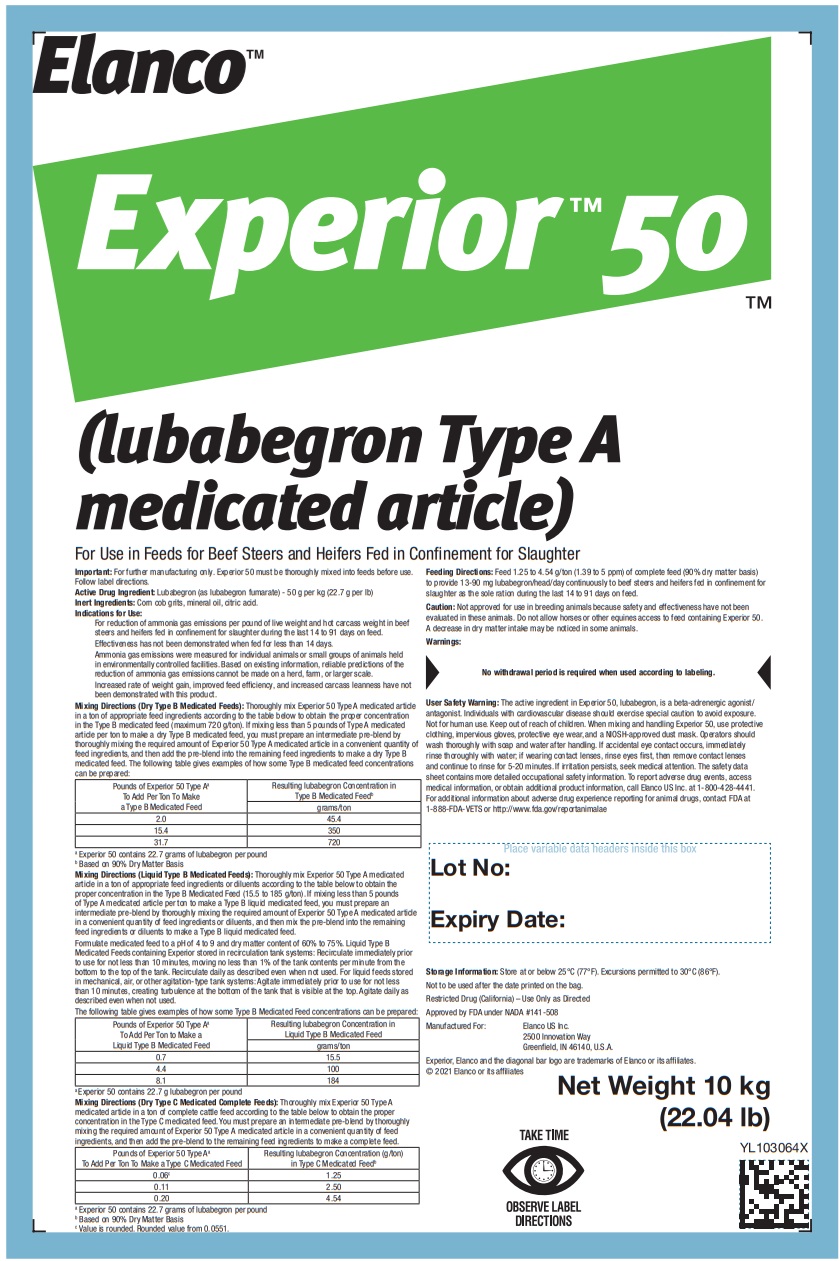 DRUG LABEL: Experior 50
NDC: 58198-5567 | Form: GRANULE
Manufacturer: Elanco US Inc.
Category: animal | Type: OTC ANIMAL DRUG LABEL
Date: 20240605

ACTIVE INGREDIENTS: Lubabegron 50 g/1 kg

Elanco™

Experior™50TM

(lubabegron Type A medicated article)

For Use in Feeds for Beef Steers and Heifers Fed in Confinement for Slaughter

Important:

For further manufacturing only. Experior 50 must be thoroughly mixed into feeds before use. Follow label directions.

Active Drug Ingredient:

Lubabegron (as lubabegron fumarate) - 50 g per kg (22.7 g per lb)

Inert Ingredients:

Corn cob grits, mineral oil, citric acid.

Indications for Use:

For reduction of ammonia gas emissions per pound of live weight and hot carcass weight in beef steers and heifers fed in confinement for slaughter during the last 14 to 91 days on feed.

Effectiveness has not been demonstrated when fed for less than 14 days.

Ammonia gas emissions were measured for individual animals or small groups of animals held in environmentally controlled facilities. Based on existing information, reliable predictions of the reduction of ammonia gas emissions cannot be made on a herd, farm, or larger scale.

Increased rate of weight gain, improved feed efficiency, and increased carcass leanness have not been demonstrated with this product.

Mixing Directions (Dry Type B Medicated Feeds):

Thoroughly mix Experior 50 Type A medicated article in a ton of appropriate feed ingredients according to the table below to obtain the proper concentration in the Type B medicated feed (maximum 720 g/ton). If mixing less than 5 pounds of Type A medicated article per ton to make a dry Type B medicated feed, you must prepare an intermediate pre-blend by thoroughly mixing the required amount of Experior 50 Type A medicated article in a convenient quantity of feed ingredients, and then add the pre-blend into the remaining feed ingredients to make a dry Type B medicated feed. The following table gives examples of how some Type B medicated feed concentrations can be prepared:

Pounds of Experior 50 Type Aa To Add Per Ton To Make a Type B Medicated Feed | Resulting lubabegron Concentration in Type B Medicated Feedb
Pounds of Experior 50 Type Aa To Add Per Ton To Make a Type B Medicated Feed | grams/ton
2.0 | 45.4
15.4 | 350
31.7 | 720
a Experior 50 contains 22.7 grams of lubabegron per pound
b Based on 90% Dry Matter Basis

Mixing Directions (Liquid Type B Medicated Feeds):

Thoroughly mix Experior 50 Type A medicated article in a ton of appropriate feed ingredients or diluents according to the table below to obtain the proper concentration in the Type B Medicated Feed (15.5 to 185 g/ton). If mixing less than 5 pounds of Type A medicated article per ton to make a Type B liquid medicated feed, you must prepare an intermediate pre-blend by thoroughly mixing the required amount of Experior 50 Type A medicated article in a convenient quantity of feed ingredients or diluents, and then mix the pre-blend into the remaining feed ingredients or diluents to make a Type B liquid medicated feed.

Formulate medicated feed to a pH of 4 to 9 and dry matter content of 60% to 75%. Liquid Type B Medicated Feeds containing Experior stored in recirculation tank systems: Recirculate immediately prior to use for not less than 10 minutes, moving no less than 1% of the tank contents per minute from the bottom to the top of the tank. Recirculate daily as described even when not used. For liquid feeds stored in mechanical, air, or other agitation-type tank systems: Agitate immediately prior to use for not less than 10 minutes, creating turbulence at the bottom of the tank that is visible at the top. Agitate daily as described even when not used.

The following table gives examples of how some Type B Medicated Feed concentrations can be prepared:

Pounds of Experior 50 Type Aa To Add Per Ton to Make a Liquid Type B Medicated Feed | Resulting lubabegron Concentration in Liquid Type B Medicated Feed
Pounds of Experior 50 Type Aa To Add Per Ton to Make a Liquid Type B Medicated Feed | grams/ton
0.7 | 15.5
4.4 | 100
8.1 | 184
a Experior 50 contains 22.7 g lubabegron per pound

Mixing Directions (Dry Type C Medicated Complete Feeds):

Thoroughly mix Experior 50 Type A medicated article in a ton of complete cattle feed according to the table below to obtain the proper concentration in the Type C medicated feed. You must prepare an intermediate pre-blend by thoroughly mixing the required amount of Experior 50 Type A medicated article in a convenient quantity of feed ingredients, and then add the pre-blend to the remaining feed ingredients to make a complete feed.

Pounds of Experior 50 Type Aa To Add Per Ton To Make a Type C Medicated Feed | Resulting lubabegron Concentration (g/ton) in Type C Medicated Feedb
0.06c | 1.25
0.11 | 2.50
0.20 | 4.54
a Experior 50 contains 22.7 grams of lubabegron per pound
b Based on 90% Dry Matter Basis
c Value is rounded. Rounded value from 0.0551.

Feeding Directions:

Feed 1.25 to 4.54 g/ton (1.39 to 5 ppm) of complete feed (90% dry matter basis) to provide 13-90 mg lubabegron/head/day continuously to beef steers and heifers fed in confinement for slaughter as the sole ration during the last 14 to 91 days on feed.

Caution:

Not approved for use in breeding animals because safety and effectiveness have not been evaluated in these animals. Do not allow horses or other equines access to feed containing Experior 50. A decrease in dry matter intake may be noticed in some animals.

Warnings:

No withdrawal period is required when used according to labeling.

User Safety Warning:

The active ingredient in Experior 50, lubabegron, is a beta-adrenergic agonist/antagonist. Individuals with cardiovascular disease should exercise special caution to avoid exposure. Not for human use. Keep out of reach of children. When mixing and handling Experior 50, use protective clothing, impervious gloves, protective eye wear, and a NIOSH-approved dust mask. Operators should wash thoroughly with soap and water after handling. If accidental eye contact occurs, immediately rinse thoroughly with water; if wearing contact lenses, rinse eyes first, then remove contact lenses and continue to rinse for 5-20 minutes. If irritation persists, seek medical attention. The safety data sheet contains more detailed occupational safety information. To report adverse drug events, access medical information, or obtain additional product information, call Elanco US Inc. at 1-800-428-4441. For additional information about adverse drug experience reporting for animal drugs, contact FDA at 1-888-FDA-VETS or http://www.fda.gov/reportanimalae

Lot No:

Expiry Date:

Storage Information:

Store at or below 25°C (77°F). Excursions permitted to 30°C (86°F).

Not to be used after the date printed on the bag.

Restricted Drug (California) – Use Only as Directed

Approved by FDA under NADA #141-508

Manufactured For:

Elanco US Inc.

2500 Innovation Way

Greenfield, IN 46140, U.S.A.

Experior, Elanco and the diagonal bar logo are trademarks of Elanco or its affiliates.

© 2021 Elanco or its affiliates

Net Weight 10 kg
(22.04 lb)

TAKE TIME

OBSERVE LABEL
DIRECTIONS

YL103064X

Principal Display Panel - 10 kg Bag Label

Elanco™

Experior™ 50 ™

(lubabegron Type A
medicated article)